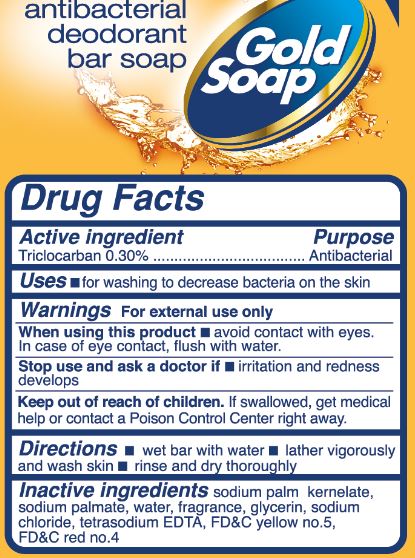 DRUG LABEL: Lucky
NDC: 20276-048 | Form: SOAP
Manufacturer: Delta Brands Inc.
Category: otc | Type: HUMAN OTC DRUG LABEL
Date: 20160418

ACTIVE INGREDIENTS: TRICLOCARBAN 0.3 g/100 g
INACTIVE INGREDIENTS: SODIUM PALM KERNELATE; SODIUM PALMITATE; WATER; GLYCERIN; SODIUM CHLORIDE; EDETATE SODIUM; FD&C YELLOW NO. 5; FD&C RED NO. 4

Drug Facts

Active Ingredient

Triclocarban 0.30%

Purpose

Antibacterial

Uses

■for hand washing to decrease bacteria on the skin

Warnings

For external use only

When using this product

■avoid contact with eyes. In case of eye contact, flush with water

Stop use and ask a doctor if

■irritation and redness develops

Keep out of reach of children

If swallowed, get medical help or contact a Poison Control Center right away.

Directions

■ wet bar with water ■ lather vigorously and wash skin ■ rinse and dry thoroughly

Inactive ingredients

sodium palm kernelate, sodium palmate, water, fragrance, glycerin, sodium chloride, tetrasodium EDTA, FD&C yellow no. 5, FD&C red no. 4